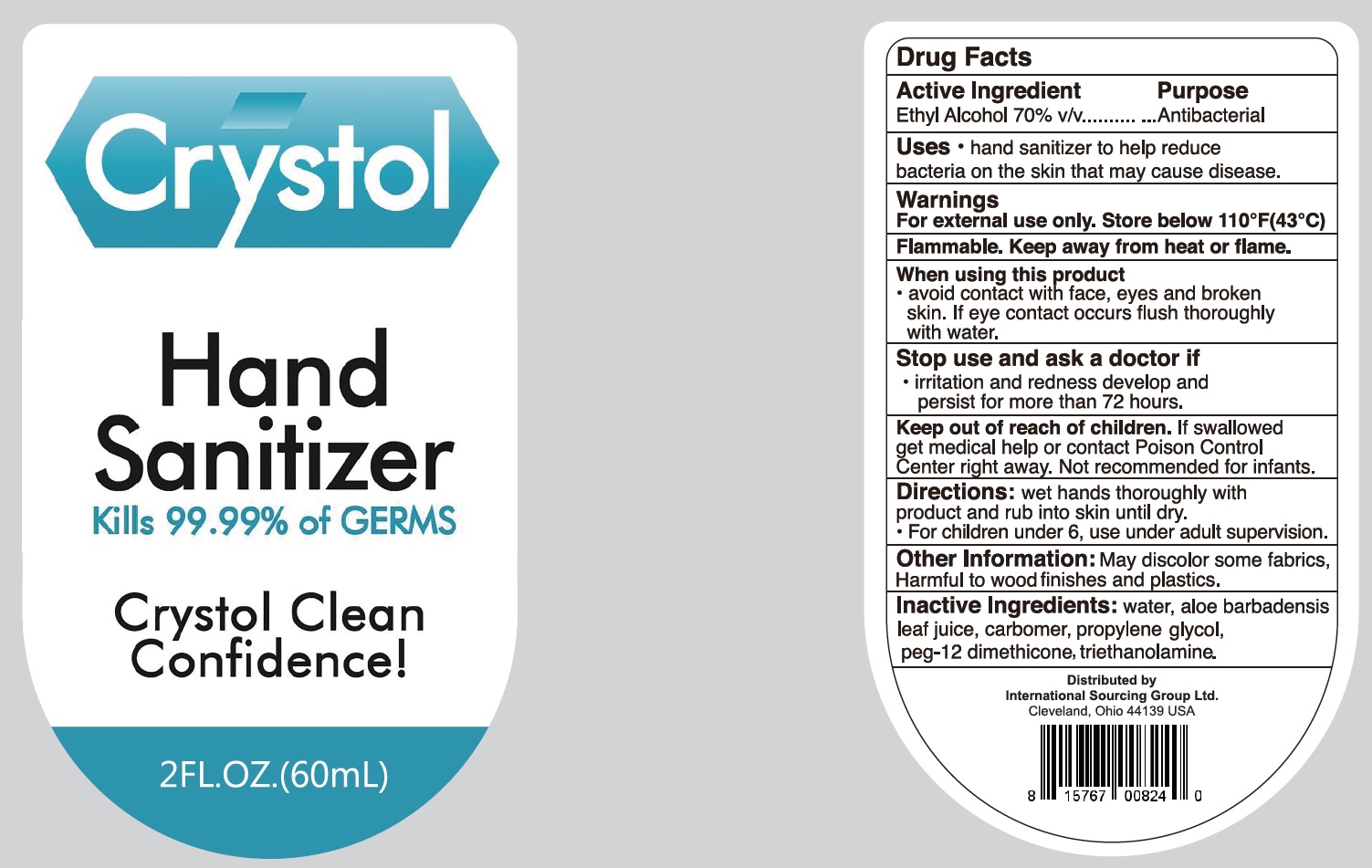 DRUG LABEL: Hand Sanitizer
NDC: 74649-003 | Form: GEL
Manufacturer: Yiwu Pharmacy Ecomm Business Enterprise Ltd
Category: otc | Type: HUMAN OTC DRUG LABEL
Date: 20200730

ACTIVE INGREDIENTS: ALCOHOL 0.7 mL/1 mL
INACTIVE INGREDIENTS: WATER; ALOE VERA LEAF; CARBOMER HOMOPOLYMER, UNSPECIFIED TYPE; PROPYLENE GLYCOL; PEG-12 DIMETHICONE; TROLAMINE

Hand Sanitizer

Active Ingredient

Ethyl Alcohol 70% v/v

Purpose

Antibacterial

Uses

- hand sanitizer to help reduce bacteria on the skin that may cause disease.

Warnings

For external use only. Store below 110°F(43°C)

Flammable. Keep away from heat or flame.

When using this product

- avoid contact with face, eyes and broken skin. If eye contact occurs flush thoroughly with water.

Stop use and ask a doctor if

- irritation and redness develop and persist for more than 72 hours.

Keep out of reach of children.

If swallowed, get medical help or contact Poison Control Center right away. Not recommended for infants.

Directions:

wet hands thoroughly with product and rub into skin until dry.

- For children under 6, use under adult supervision.

Other Information:

May discolor some fabrics, Harmful to wood finishes and plastics.

Inactive Ingredients:

water, aloe barbadensis leaf juice, carbomer, propylene glycol, peg-12 dimethicone, triethanolamine.